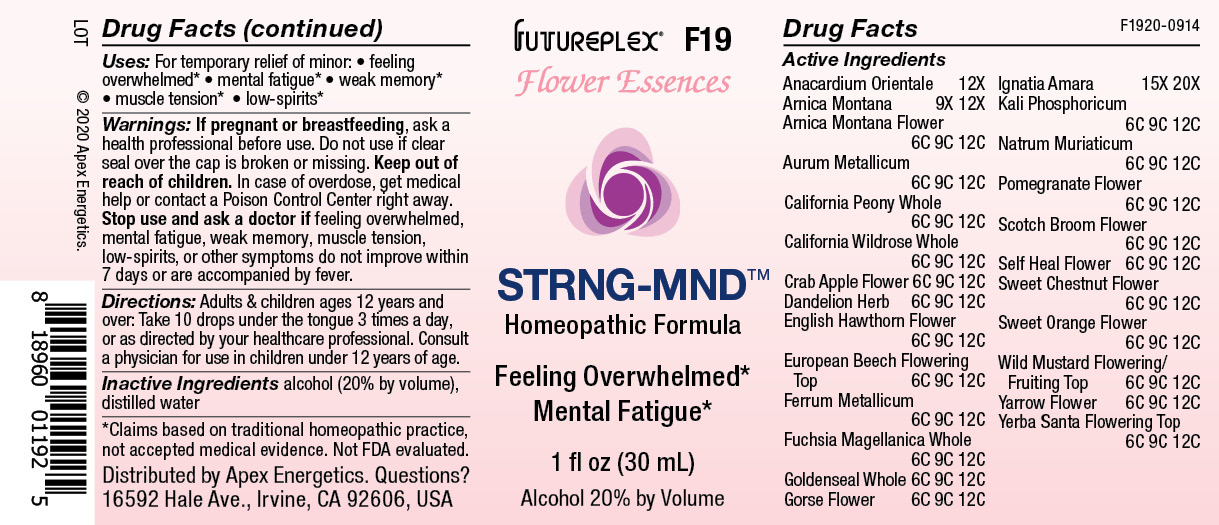 DRUG LABEL: F19
NDC: 63479-0619 | Form: SOLUTION/ DROPS
Manufacturer: Apex Energetics Inc.
Category: homeopathic | Type: HUMAN OTC DRUG LABEL
Date: 20240108

ACTIVE INGREDIENTS: ARNICA MONTANA FLOWER 12 [hp_C]/1 mL; IRON 12 [hp_C]/1 mL; STRYCHNOS IGNATII SEED 20 [hp_X]/1 mL; SODIUM CHLORIDE 12 [hp_C]/1 mL; PUNICA GRANATUM FLOWER 12 [hp_C]/1 mL; SINAPIS ARVENSIS FLOWERING/FRUITING TOP 12 [hp_C]/1 mL; ACHILLEA MILLEFOLIUM FLOWER 12 [hp_C]/1 mL; PAEONIA CALIFORNICA WHOLE 12 [hp_C]/1 mL; MALUS SYLVESTRIS FLOWER 12 [hp_C]/1 mL; PRUNELLA VULGARIS FLOWER 12 [hp_C]/1 mL; CASTANEA SATIVA FLOWER 12 [hp_C]/1 mL; CITRUS SINENSIS FLOWER 12 [hp_C]/1 mL; TARAXACUM OFFICINALE FLOWERING TOP 12 [hp_C]/1 mL; ULEX EUROPAEUS FLOWER 12 [hp_C]/1 mL; POTASSIUM PHOSPHATE, DIBASIC 12 [hp_C]/1 mL; CYTISUS SCOPARIUS FLOWER 12 [hp_C]/1 mL; ERIODICTYON CALIFORNICUM FLOWERING TOP 12 [hp_C]/1 mL; CRATAEGUS MONOGYNA FLOWER 12 [hp_C]/1 mL; HYDRASTIS CANADENSIS WHOLE 12 [hp_C]/1 mL; SEMECARPUS ANACARDIUM JUICE 12 [hp_X]/1 mL; ARNICA MONTANA 12 [hp_X]/1 mL; GOLD 12 [hp_C]/1 mL; ROSA CALIFORNICA WHOLE 12 [hp_C]/1 mL; FAGUS SYLVATICA FLOWERING TOP 12 [hp_C]/1 mL; FUCHSIA MAGELLANICA WHOLE 12 [hp_C]/1 mL
INACTIVE INGREDIENTS: WATER; ALCOHOL

F19

Active Ingredients
Anacardium Orientale | 12X
Arnica Montana | 9X 12X
Arnica Montana Flower | 6C 9C 12C
Aurum Metallicum | 6C 9C 12C
California Peony Whole | 6C 9C 12C
California Wildrose Whole | 6C 9C 12C
Crab Apple Flower | 6C 9C 12C
Dandelion Herb | 6C 9C 12C
English Hawthron Flower | 6C 9C 12C
European Beech Flowering Top | 6C 9C 12C
Ferrum Metallicum | 6C 9C 12C
Fuchsia Magellanica Whole | 6C 9C 12C
Goldenseal Whole | 6C 9C 12C
Gorse Flower | 6C 9C 12C
Ignatia Amara | 15X 20X
Kali Phosphoricum | 6C 9C 12C
Natrum Muriaticum | 6C 9C 12C
Pomegranate Flower | 6C 9C 12C
Scotch Broom Flower | 6C 9C 12C
Self Heal Flower | 6C 9C 12C
Sweet Chestnut Flower | 6C 9C 12C
Sweet Orange Flower | 6C 9C 12C
Wild Mustard Flowering/Fruiting Top | 6C 9C 12C
Yarrow Flower | 6C 9C 12C
Yerba Santa Flowering Top | 6C 9C 12C

INDICATIONS AND USAGE

Uses:

For temporary relief of minor:

feeling overwhelmed*

mental fatigue*

weak memory*

muscle tension*

low-spirits*

*Claims based on traditional homeopathic practice, not accepted medical evidence. Not FDA evaluated.

Warnings:

PREGNANCY OR BREAST FEEDING

If pregnant or breastfeeding, ask a health professional before use.

Do not use if clear seal over the cap is broken or missing.

Keep out of reach of children. In case of overdose, get medical help or contact a Poison Control Center right away.

Stop use and ask a doctor if feeling overwhelmed, mental fatigue, weak memory, muscle tension, low-spirits, or other symptoms do not improve within 7 days or are accompanied by fever.

Directions:

Adults & children ages 12 years and over: Take 10 drops under the tongue 3 times a day, or as directed by your healthcare professional. Consult a physician for use in children under 12 years of age

Inactive Ingredients

alcohol (20% by volume), distilled water

Distributed by Apex Energetics. Questions?

16592 Hale Ave., Irvine, CA 92606, USA

PACKAGE LABEL

FUTUREPLEX® F19

FLOWER ESSENCES

STRNG-MND™

Homeopathic Formula

Feeling Overwhelmed*

Mental Fatigue*

1 fl oz (30 mL)

Alcohol 20% by Volume